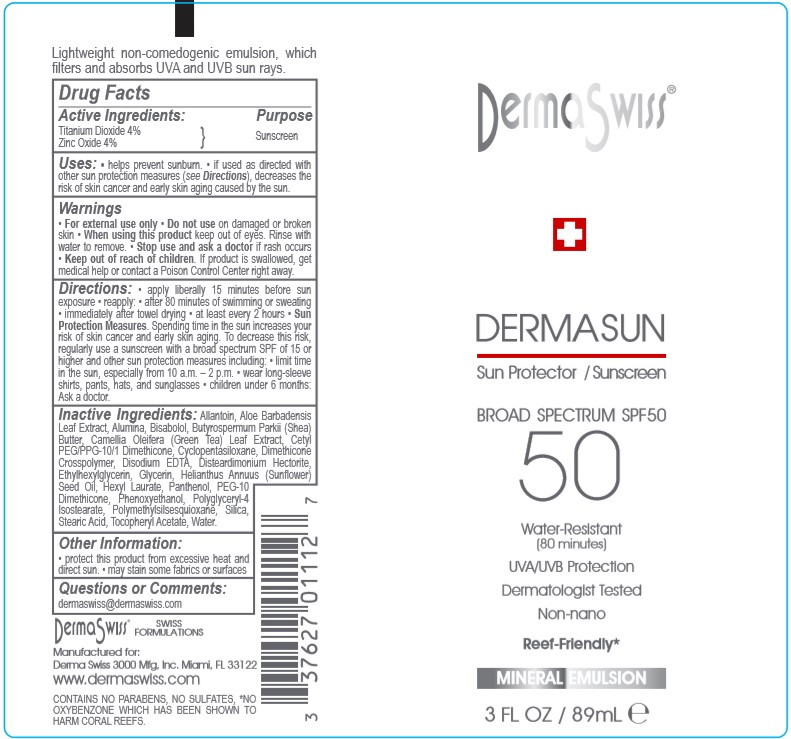 DRUG LABEL: Infinitek
NDC: 58443-0363 | Form: LOTION
Manufacturer: Prime Enterprises Inc.
Category: otc | Type: HUMAN OTC DRUG LABEL
Date: 20201002

ACTIVE INGREDIENTS: TITANIUM DIOXIDE 42.4 mg/1 mL; ZINC OXIDE 42.4 mg/1 mL
INACTIVE INGREDIENTS: EVENING PRIMROSE OIL; PHYSALIS ANGULATA; ROSA CANINA SEED; TRIETHOXYCAPRYLYLSILANE; PHENOXYETHANOL; SILICON DIOXIDE; CAMELLIA OLEIFERA LEAF; POLYMETHYLSILSESQUIOXANE (4.5 MICRONS); .ALPHA.-TOCOPHEROL ACETATE; ALLANTOIN; ETHYLHEXYLGLYCERIN; PEG-10 DIMETHICONE (600 CST); SHEA BUTTER; WATER; CETYL PEG/PPG-10/1 DIMETHICONE (HLB 2); DIMETHICONE CROSSPOLYMER (450000 MPA.S AT 12% IN CYCLOPENTASILOXANE); DISTEARDIMONIUM HECTORITE; GLYCERIN; HEXYL LAURATE; POLYGLYCERYL-4 ISOSTEARATE; STEARIC ACID; CYCLOMETHICONE 5; ALUMINUM OXIDE; ANACYSTIS NIDULANS EXTRACT; FERRIC OXIDE RED; LINSEED OIL; MEDIUM-CHAIN TRIGLYCERIDES; CUCUMBER

IINFINITEK PARIS Broad Spectrum SPF 50 Mineral Face Lotion

Active ingredients

Titanium Dioxide 4 %

Zinc Oxide 4 %

Purpose

Sunscreen

Uses:

- helps prevent sunburn
- if used as directed with other sun protection measures (see Directions), decreases the risk of skin cancer and early skin aging caused by the sun

Warnings

For external use only

Do not use on damaged or broken skin

When using this product keep out of eyes. Rinse with water to remove.

Stop use and ask a doctor if rash occurs

Keep out of reach of children. If product is swallowed, get medical help or contact a Poison Control Center right away.

Directions

- apply liberally 15 minutes before sun exposure
- reapply:
- after 80 minutes of swimming or sweating
- immediately after towel drying
- at least every 2 hours
- Sun Protection Measures. Spending time in the sun increases your risk of skin cancer and early skin aging. To decrease this risk, regularly use a sunscreen with broad spectrum SPF of 15 or higher and other sun protection measures including:
- limit time in the sun, especially from 10 a.m. – 2 p.m.
- wear long-sleeve shirts, pants, hats, and sunglasses
- children under 6 months: Ask a doctor

Inactive ingredients:

Allantoin, Aloe Barbadensis Leaf Extract, Alumina, Bisabolol, Butyrospermum Parkii (Shea) Butter, Camellia Oleifera (Green Tea) Leaf Extract, Cetyl PEG/PPG-10/1 Dimethicone, Cyclopentasiloxane, Dimethicone Crosspolymer, Disodium EDTA, Disteardimonium Hectorite, Ethylhexylglycerin, Glycerin, Helianthus Annuus (Sunflower) Seed Oil, Hexyl Laurate, Panthenol, PEG-10 Dimethicone, Phenoxyethanol, Polyglyceryl-4 Isostearate, Polymethylsilsesquioxane, Silica, Stearic Acid, Tocopheryl Acetate, Water

Other information

- protect this product from excessive heat and direct sun
- may stain some fabrics or surfaces

Questions or comments?

dermaswiss@dermaswiss.com